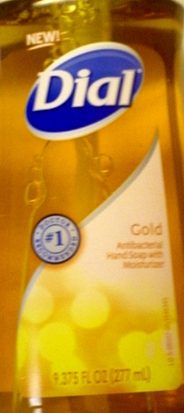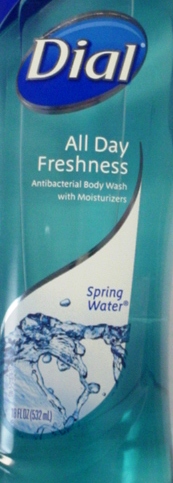 DRUG LABEL: All Day Freshness Antibacterial Body Wash with Moisturizer
NDC: 50945-001 | Form: SOLUTION
Manufacturer: Diversapack of Monroe, LLC
Category: otc | Type: HUMAN OTC DRUG LABEL
Date: 20100603

ACTIVE INGREDIENTS: Triclosan 0.15 g/100 g

Drug Facts

Active Ingredient- Triclosan 0.15%

Purpose- Antibacterial

PURPOSE

Uses - for washing to decrease bacteria on the skin

Warnings - For external use only
When using this product - avoid contact with eyes. In case of eye contact,flush with water
Stop use and ask a doctor if - irritation and redness develops.

Keep out of reach of children- If swallowed, get medical help or contact a Poison Control Center right away.

WHEN USING

Directions - Squeeze onto wet hands or body sponge. Work into a lather. Wash skin,rinse and dry thoroughly.

INACTIVE INGREDIENT

Inactive Ingredients Water, Sodium Laureth Sulfate, Cocamidoproyl betaine, PEG-8, fragrance, glycerin, Polyquaternium-10, Cocamidopropyl PG-dimonium chloride, isostearamidopropyl morpholine lactate, Sodium Chloride, DMDM hydantoin,Citric Acid, tetrasodium EDTA, blue 1, Red 33.

Questions?1-800-258-Dial (3425)

Active Ingredient -Triclosan 0.15%
Purpose - Antibacterial

PURPOSE

Uses- for handwashing to decrease bacteria on the skin

Warnings-For external use only
When using this product - avoid contact with eyes. In case of eye contact,flush with water
Stop use and ask a doctor if - irritation and redness develops.

Keep out of reach of children- If swallowed, get medical help or contact a Poison Control Center right away.

Directions

- pump into hands wet as needed.

- lather vigorously for at least 15 seconds

- wash skin, rinse thoroughly and dry

INACTIVE INGREDIENT

Inactive ingredients: Water, Sodium Laureth Sulfate,Cocamidopropyl Betaine, Sodium Chloride, Cocamidopropyl Hydroxysultaine, Glycerin,Fragrance, Polyquaternium-7, PPG-2 Hydroxyethyl Coco/ISostearamide, DMDM Hydantoin,Tetrasodium EDTA,Citric Acid, Yellow 5, Red 4

Questions? 1-800-258-Dial (3425)